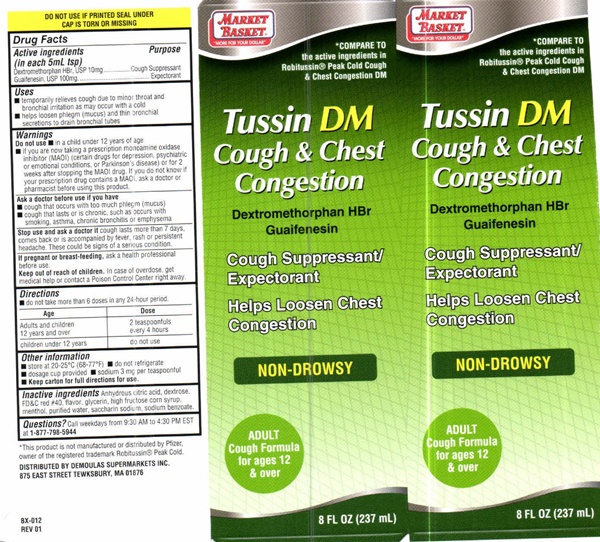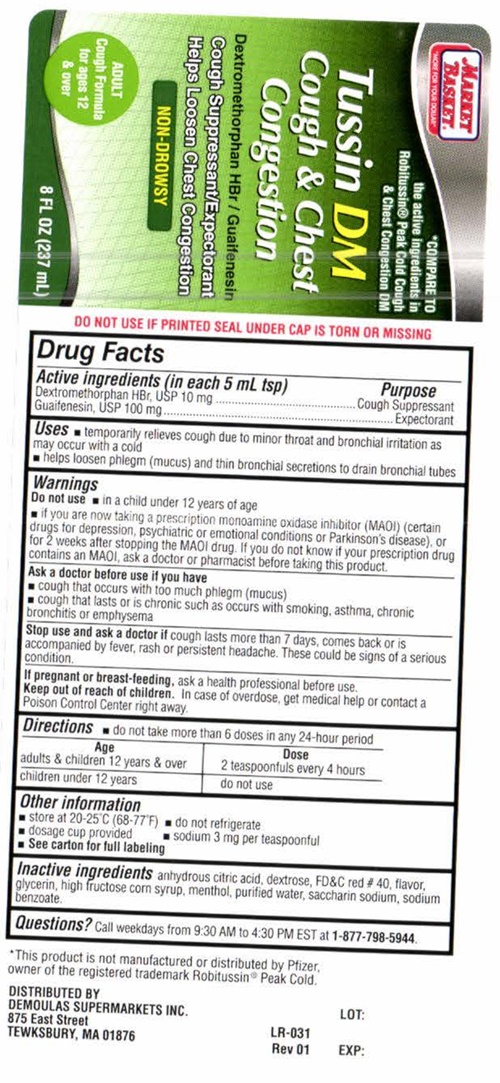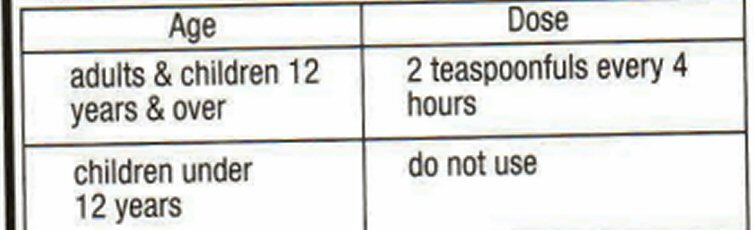 DRUG LABEL: Tussin DM
NDC: 53942-503 | Form: LIQUID
Manufacturer: DeMoulas Market Basket
Category: otc | Type: HUMAN OTC DRUG LABEL
Date: 20231229

ACTIVE INGREDIENTS: DEXTROMETHORPHAN HYDROBROMIDE 10 mg/5 mL; GUAIFENESIN 100 mg/5 mL
INACTIVE INGREDIENTS: CITRIC ACID MONOHYDRATE; DEXTROSE; FD&C RED NO. 40; GLYCERIN; HIGH FRUCTOSE CORN SYRUP; MENTHOL; WATER; SACCHARIN SODIUM; SODIUM BENZOATE

Tussin DM 503

Drug Facts Active ingredients (in each 5 mL tsp)

Dextromethorphan HBr, USP 10 mg
Guaifenesin, USP 100 mg

Purpose

Cough Suppressant
Expectorant

Keep out of reach of children

In case of overdose, get medical help or contact a Poison Control Center right away.

Uses

- temporarily relieves cough due to minor throat and bronchial irritation as may occur with a cold
- helps loosen phlegm (mucus) and thin bronchial secretions to drain bronchial tubes

Warnings

Do not use

- in a child under 12 years of age
- if you are now taking a prescription monoamine oxidase inhibitor (MAOI) (certain drugs for depression, psychiatric, or emotional conditions, or Parkinson's disease), or for 2 weeks after stopping the MAOI drug. If you do not know if your prescription drug contains an MAOI, ask a doctor or pharmacist before taking this product.

Ask a doctor before use if you have

- cough that occurs with too much phlegm mucus)
- cough that lasts or is chronic such as occurs with smoking, asthma, chronic bronchitis or emphysema

Stop use and ask a doctor if

- cough lasts more than 7 days, comes back, or is accompanied by fever, rash, or persistent headache.
  These could be signs of a serious condition.

If pregnant or breast-feeding

ask a health professional before use.

Directions

- do not take more than 6 doses in any 24-hour period

Other information

- Keep carton for full Direction for use.

- store at 20‐25 ° C (68‐77 ° F)
- do not refrigerate
- dosage cup provided
- sodium 3 mg per teaspoonful

Inactive ingredients

anhydrous citric acid, dextrose, FD and C red no. 40, flavor, glycerin, high fructose corn syrup, purified water, saccharin sodium, sodium benzoate

Questions?

Call weekdays from 9:30 AM to 4:30 PM EST at
1-877-798-5944

Product Label

"MORE FOR YOUR DOLLAR"
MARKET BASKET®
*COMPARE TO THE ACTIVE INGREDIENTS IN ROBITUSSIN® PEAK COLD COUGH and CHEST CONGESTION DM
Tussin DM

Cough and Chest Congestion

Dextromethorphan HBr
Guaifenesin

COUGH SUPPRESSANT /
EXPECTORANT

Helps to Loosen Chest Congestion

NON-DROWSY

ADULT
Cough Formula

for ages 12 and over

8 FL OZ (237 mL)
DO NOT USE IF IMPRINTED SHRINK BAND IS MISSING OR BROKEN
*This product is not manufactured or distributed by Pfizer, owner of the registered trademark Robitussin® Peak Cold.
Distributed by: DEMOULAS SUPERMARKETS INC.
875 EAST STREET - TEWKSBURY, MA 01876
BX-012 REV 01

res